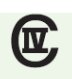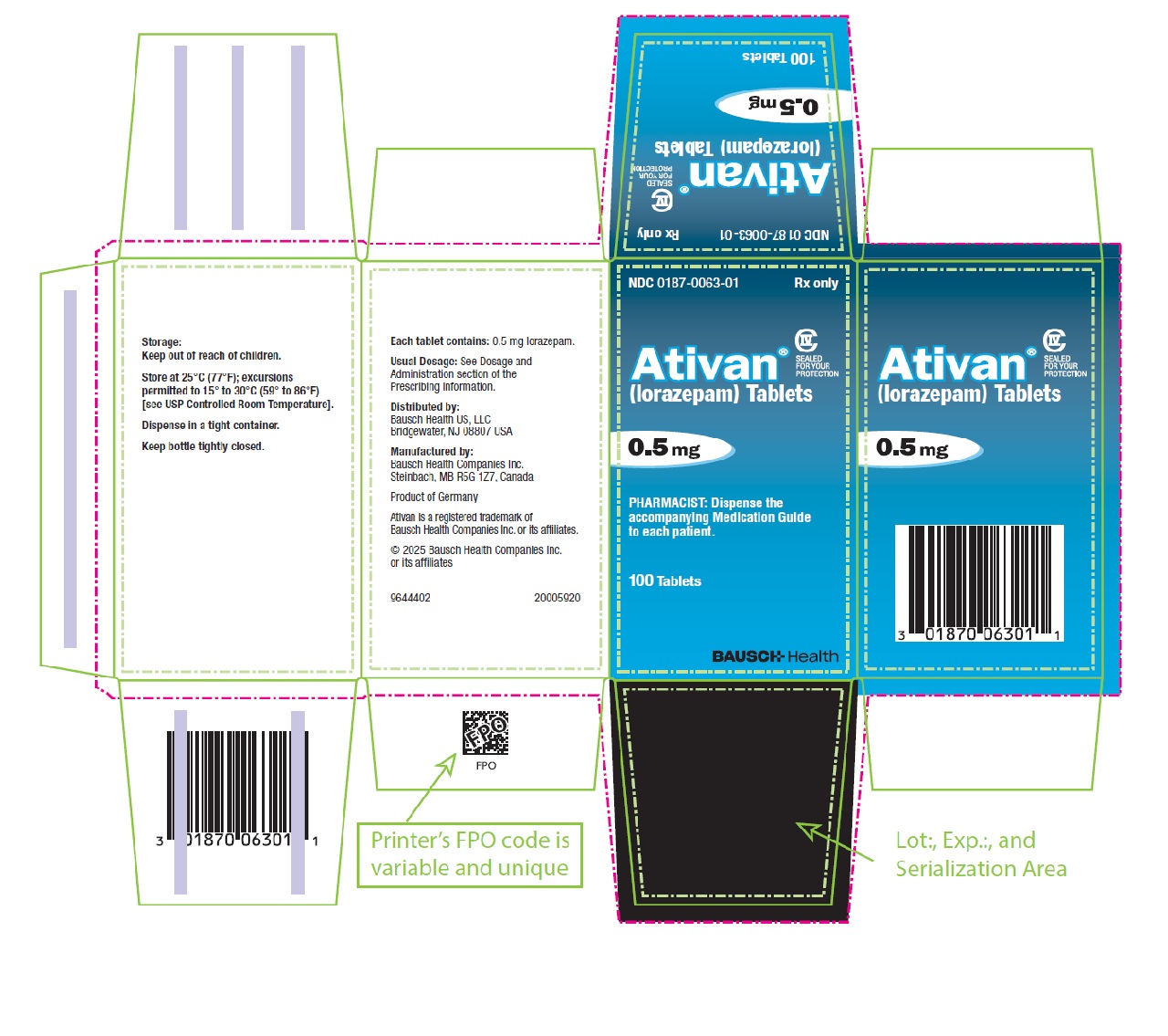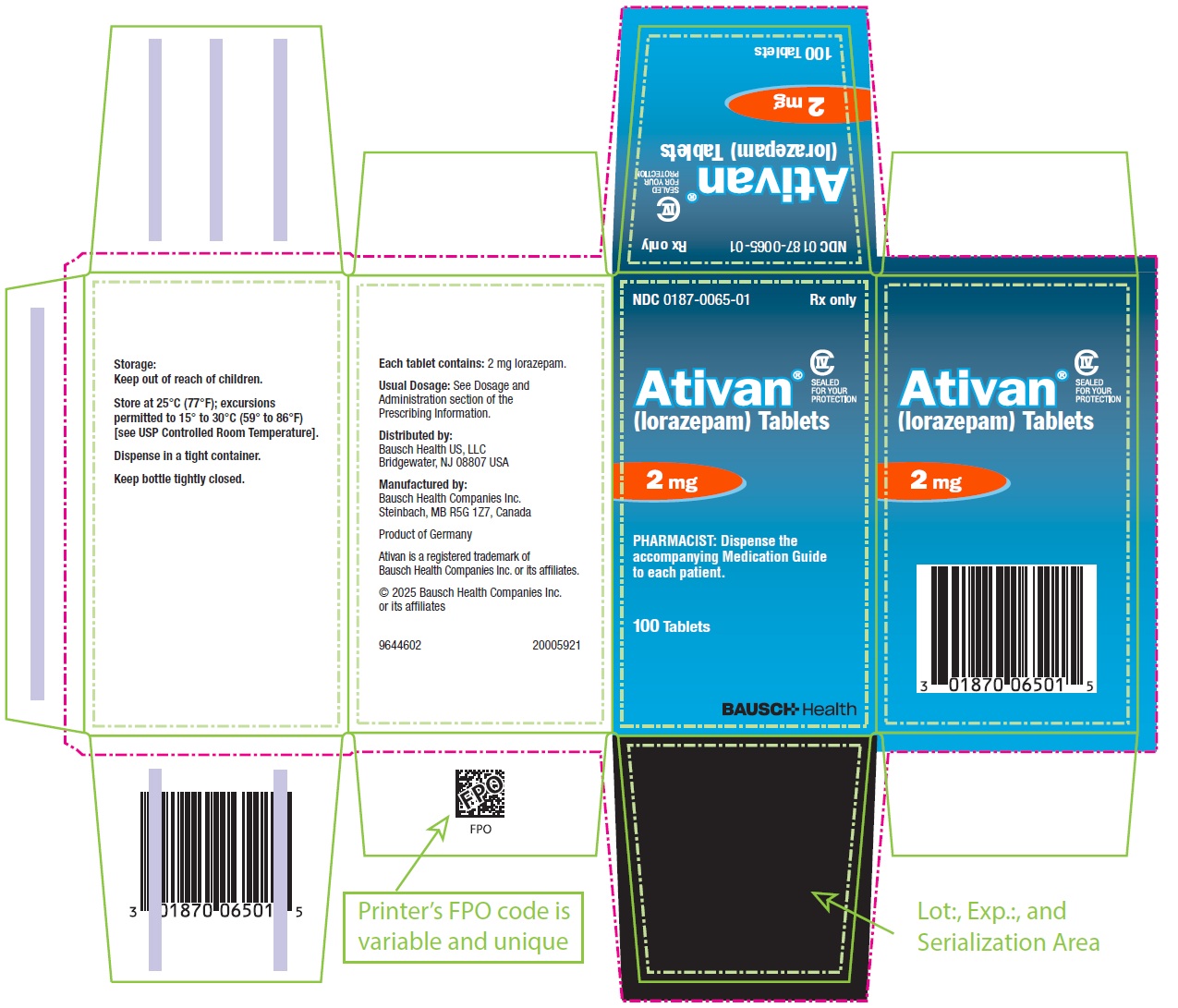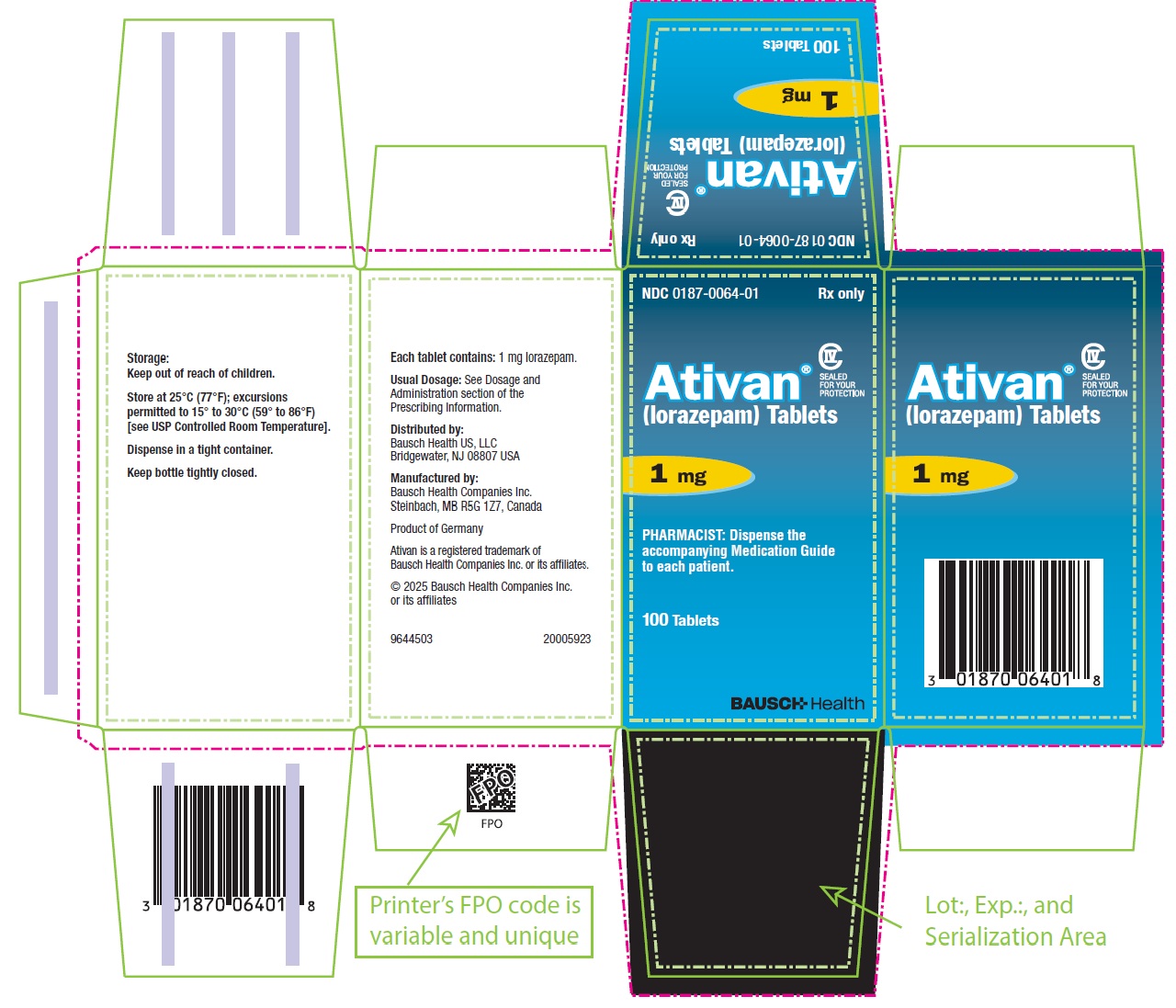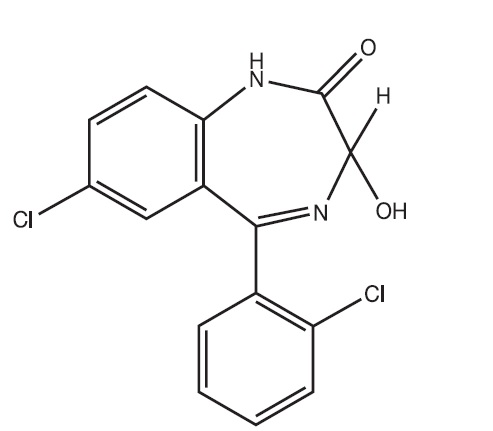 DRUG LABEL: Ativan
NDC: 0187-0063 | Form: TABLET
Manufacturer: Bausch Health US LLC
Category: prescription | Type: HUMAN PRESCRIPTION DRUG LABEL
Date: 20250709
DEA Schedule: CIV

ACTIVE INGREDIENTS: LORAZEPAM 0.5 mg/1 1
INACTIVE INGREDIENTS: LACTOSE MONOHYDRATE; MAGNESIUM STEARATE; POLACRILIN POTASSIUM; MICROCRYSTALLINE CELLULOSE

Ativan®
(lorazepam)

Tablets

WARNING: RISKS FROM CONCOMITANT USE WITH OPIOIDS; ABUSE, MISUSE, AND ADDICTION; and DEPENDENCE AND WITHDRAWAL REACTIONS

- Concomitant use of benzodiazepines and opioids may result in profound sedation, respiratory depression, coma, and death. Reserve concomitant prescribing of these drugs for patients for whom alternative treatment options are inadequate. Limit dosages and durations to the minimum required. Follow patients for signs and symptoms of respiratory depression and sedation (see WARNINGS and PRECAUTIONS).
- The use of benzodiazepines, including Ativan, exposes users to risks of abuse, misuse, and addiction, which can lead to overdose or death. Abuse and misuse of benzodiazepines commonly involve concomitant use of other medications, alcohol, and/or illicit substances, which is associated with an increased frequency of serious adverse outcomes. Before prescribing Ativan and throughout treatment, assess each patient’s risk for abuse, misuse, and addiction (see WARNINGS).
- The continued use of benzodiazepines, including Ativan, may lead to clinically significant physical dependence. The risks of dependence and withdrawal increase with longer treatment duration and higher daily dose. Abrupt discontinuation or rapid dosage reduction of Ativan after continued use may precipitate acute withdrawal reactions, which can be life-threatening. To reduce the risk of withdrawal reactions, use a gradual taper to discontinue ATIVAN or reduce the dosage (see DOSAGE AND ADMINISTRATION and WARNINGS).

DESCRIPTION

Ativan (lorazepam), an antianxiety agent, has the chemical formula, 7-chloro-5-(o-chlorophenyl)-1,3-dihydro-3-hydroxy-2H-1,4-benzodiazepin-2-one:

C15H10Cl2N2O2 M.W. 321.16

It is a nearly white powder almost insoluble in water. Each Ativan (lorazepam) tablet, to be taken orally, contains 0.5 mg, 1 mg, or 2 mg of lorazepam. The inactive ingredients present are lactose monohydrate, magnesium stearate, microcrystalline cellulose, and polacrilin potassium.

CLINICAL PHARMACOLOGY

Studies in healthy volunteers show that in single high doses Ativan (lorazepam) has a tranquilizing action on the central nervous system with no appreciable effect on the respiratory or cardiovascular systems.

Ativan (lorazepam) is readily absorbed with an absolute bioavailability of 90%. Peak concentrations in plasma occur approximately 2 hours following administration. The peak plasma level of lorazepam from a 2 mg dose is approximately 20 ng/mL.

The mean half-life of unconjugated lorazepam in human plasma is about 12 hours and for its major metabolite, lorazepam glucuronide, about 18 hours. At clinically relevant concentrations, lorazepam is approximately 85% bound to plasma proteins. Ativan (lorazepam) is rapidly conjugated at its 3-hydroxy group into lorazepam glucuronide which is then excreted in the urine. Lorazepam glucuronide has no demonstrable central nervous system (CNS) activity in animals.

The plasma levels of lorazepam are proportional to the dose given. There is no evidence of accumulation of lorazepam on administration up to 6 months.

Studies comparing young and elderly subjects have shown that advancing age does not have a significant effect on the pharmacokinetics of lorazepam. However, in one study involving single intravenous doses of 1.5 to 3 mg of Ativan Injection, mean total body clearance of lorazepam decreased by 20% in 15 elderly subjects of 60 to 84 years of age compared to that in 15 younger subjects of 19 to 38 years of age.

INDICATIONS AND USAGE

Ativan (lorazepam) is indicated for the management of anxiety disorders or for the short-term relief of the symptoms of anxiety or anxiety associated with depressive symptoms. Anxiety or tension associated with the stress of everyday life usually does not require treatment with an anxiolytic.

The effectiveness of Ativan (lorazepam) in long-term use, that is, more than 4 months, has not been assessed by systematic clinical studies. The physician should periodically reassess the usefulness of the drug for the individual patient.

CONTRAINDICATIONS

Ativan (lorazepam) is contraindicated in patients with:

- hypersensitivity to benzodiazepines or to any components of the formulation
- acute narrow-angle glaucoma.

WARNINGS

Risks from Concomitant Use with Opioids

Concomitant use of benzodiazepines, including Ativan, and opioids may result in profound sedation, respiratory depression, coma, and death. Because of these risks, reserve concomitant prescribing of these drugs in patients for whom alternative treatment options are inadequate. Observational studies have demonstrated that concomitant use of opioid analgesics and benzodiazepines increases the risk of drug-related mortality compared to use of opioids alone. If a decision is made to prescribe Ativan concomitantly with opioids, prescribe the lowest effective dosages and minimum durations of concomitant use, and follow patients closely for signs and symptoms of respiratory depression and sedation. In patients already receiving an opioid analgesic, prescribe a lower initial dose of Ativan than indicated in the absence of an opioid and titrate based on clinical response. If an opioid is initiated in a patient already taking Ativan, prescribe a lower initial dose of the opioid and titrate based upon clinical response.

Advise both patients and caregivers about the risks of respiratory depression and sedation when Ativan is used with opioids. Advise patients not to drive or operate heavy machinery until the effects of concomitant use with the opioid have been determined (see PRECAUTIONS: Drug Interactions).

Abuse, Misuse, and Addiction

The use of benzodiazepines, including Ativan, exposes users to the risks of abuse, misuse, and addiction, which can lead to overdose or death. Abuse and misuse of benzodiazepines often (but not always) involve the use of doses greater than the maximum recommended dosage and commonly involve concomitant use of other medications, alcohol, and/or illicit substances, which is associated with an increased frequency of serious adverse outcomes, including respiratory depression, overdose, or death (see DRUG ABUSE AND DEPENDENCE: Abuse).

Before prescribing Ativan and throughout treatment, assess each patient’s risk for abuse, misuse, and addiction (e.g., using a standardized screening tool). Use of Ativan, particularly in patients at elevated risk, necessitates counseling about the risks and proper use of Ativan along with monitoring for signs and symptoms of abuse, misuse, and addiction. Prescribe the lowest effective dosage; avoid or minimize concomitant use of CNS depressants and other substances associated with abuse, misuse, and addiction (e.g., opioid analgesics, stimulants); and advise patients on the proper disposal of unused drug. If a substance use disorder is suspected, evaluate the patient and institute (or refer them for) early treatment, as appropriate.

Dependence and Withdrawal Reactions

To reduce the risk of withdrawal reactions, use a gradual taper to discontinue Ativan or reduce the dosage (a patient-specific plan should be used to taper the dose) (see DOSAGE AND ADMINISTRATION: Discontinuation or Dosage Reduction of Ativan).

Patients at an increased risk of withdrawal adverse reactions after benzodiazepine discontinuation or rapid dosage reduction include those who take higher dosages, and those who have had longer durations of use.

Acute Withdrawal Reactions

The continued use of benzodiazepines, including Ativan, may lead to clinically significant physical dependence. Abrupt discontinuation or rapid dosage reduction of Ativan after continued use, or administration of flumazenil (a benzodiazepine antagonist) may precipitate acute withdrawal reactions, which can be life-threatening (e.g., seizures) (see DRUG ABUSE AND DEPENDENCE: Dependence).

Protracted Withdrawal Syndrome

In some cases, benzodiazepine users have developed a protracted withdrawal syndrome with withdrawal symptoms lasting weeks to more than 12 months (see DRUG ABUSE AND DEPENDENCE: Dependence).

Pre-existing depression may emerge or worsen during use of benzodiazepines including lorazepam. Ativan (lorazepam) is not recommended for use in patients with a primary depressive disorder or psychosis.

Use of benzodiazepines, including lorazepam, both used alone and in combination with other CNS depressants, may lead to potentially fatal respiratory depression (see PRECAUTIONS: Drug Interactions).

As with all patients on CNS-depressant drugs, patients receiving lorazepam should be warned not to operate dangerous machinery or motor vehicles and that their tolerance for alcohol and other CNS depressants will be diminished.

Neonatal Sedation and Withdrawal Syndrome

Use of Ativan late in pregnancy can result in sedation (respiratory depression, lethargy, hypotonia) and/or withdrawal symptoms (hyperreflexia, irritability, restlessness, tremors, inconsolable crying, and feeding difficulties) in the neonate (see PRECAUTIONS: Pregnancy). Monitor neonates exposed to Ativan during pregnancy or labor for signs of sedation and monitor neonates exposed to Ativan during pregnancy for signs of withdrawal; manage these neonates accordingly.

PRECAUTIONS

In patients with depression, a possibility for suicide should be borne in mind; benzodiazepines should not be used in such patients without adequate antidepressant therapy.

Lorazepam should be used with caution in patients with compromised respiratory function (e.g., COPD, sleep apnea syndrome).

Elderly or debilitated patients may be more susceptible to the sedative effects of lorazepam. Therefore, these patients should be monitored frequently and have their dosage adjusted carefully according to patient response; the initial dosage should not exceed 2 mg.

Paradoxical reactions have been occasionally reported during benzodiazepine use. Such reactions may be more likely to occur in children and the elderly. Should these occur, use of the drug should be discontinued.

The usual precautions for treating patients with impaired renal or hepatic function should be observed. As with all benzodiazepines, the use of lorazepam may worsen hepatic encephalopathy; therefore, lorazepam should be used with caution in patients with severe hepatic insufficiency and/or encephalopathy. Dosage for patients with severe hepatic insufficiency should be adjusted carefully according to patient response; lower doses may be sufficient in such patients.

In patients where gastrointestinal or cardiovascular disorders coexist with anxiety, it should be noted that lorazepam has not been shown to be of significant benefit in treating the gastrointestinal or cardiovascular component.

Esophageal dilation occurred in rats treated with lorazepam for more than 1 year at 6 mg/kg/day. The no-effect dose was 1.25 mg/kg/day (approximately 6 times the maximum human therapeutic dose of 10 mg/day). The effect was reversible only when the treatment was withdrawn within 2 months of first observation of the phenomenon. The clinical significance of this is unknown. However, use of lorazepam for prolonged periods and in geriatric patients requires caution, and there should be frequent monitoring for symptoms of upper GI disease.

Safety and effectiveness of Ativan (lorazepam) in children of less than 12 years have not been established.

Information for Patients

Advise the patient to read the FDA-approved patient labeling (Medication Guide).

Risks from Concomitant Use with Opioids

Advise both patients and caregivers about the risks of potentially fatal respiratory depression and sedation when Ativan is used with opioids and not to use such drugs concomitantly unless supervised by a healthcare provider. Advise patients not to drive or operate heavy machinery until the effects of concomitant use with the opioid have been determined (see WARNINGS: Risks from Concomitant Use of Opioids and PRECAUTIONS: Drug Interactions).

Abuse, Misuse, and Addiction

Inform patients that the use of Ativan even at recommended doses, exposes users to risks of abuse, misuse, and addiction, which can lead to overdose and death, especially when used in combination with other medications (e.g., opioid analgesics), alcohol, and/or illicit substances. Inform patients about the signs and symptoms of benzodiazepine abuse, misuse, and addiction; to seek medical help if they develop these signs and/or symptoms; and on the proper disposal of unused drug (see WARNINGS: Abuse Misuse, and Addiction and DRUG ABUSE AND DEPENDENCE).

Withdrawal Reactions

Inform patients that the continued use of Ativan may lead to clinically significant physical dependence and that abrupt discontinuation or rapid dosage reduction of Ativan may precipitate acute withdrawal reactions, which can be life-threatening. Inform patients that in some cases, patients taking benzodiazepines have developed a protracted withdrawal syndrome with withdrawal symptoms lasting weeks to more than 12 months. Instruct patients that discontinuation or dosage reduction of Ativan may require a slow taper (see WARNINGS: Dependence and Withdrawal Reactions and DRUG ABUSE AND DEPENDENCE).

Pregnancy

Advise pregnant females that use of Ativan late in pregnancy can result in sedation (respiratory depression, lethargy, hypotonia) and/or withdrawal symptoms (hyperreflexia, irritability, restlessness, tremors, inconsolable crying, and feeding difficulties) in newborns (see WARNINGS: Neonatal Sedation and Withdrawal Syndrome and PRECAUTIONS: Pregnancy). Instruct patients to inform their healthcare provider if they are pregnant.

Advise patients that there is a pregnancy exposure registry that monitors pregnancy outcomes in women exposed to Ativan during pregnancy (see PRECAUTIONS: Pregnancy).

Nursing

Instruct patients to notify their healthcare provider if they are breastfeeding or intend to breastfeed. Instruct breastfeeding patients using Ativan to monitor infants for excessive sedation, poor feeding and poor weight gain, and to seek medical attention if they notice these signs (see PRECAUTIONS: Nursing Mothers).

Essential Laboratory Tests

Some patients on Ativan (lorazepam) have developed leukopenia, and some have had elevations of LDH. As with other benzodiazepines, periodic blood counts and liver function tests are recommended for patients on long-term therapy.

Drug Interactions

The concomitant use of benzodiazepines and opioids increases the risk of respiratory depression because of actions at different receptor sites in the CNS that control respiration. Benzodiazepines interact at GABAA sites and opioids interact primarily at mu receptors. When benzodiazepines and opioids are combined, the potential for benzodiazepines to significantly worsen opioid-related respiratory depression exists. Limit dosage and duration of concomitant use of benzodiazepines and opioids, and monitor patients closely for respiratory depression and sedation.

The benzodiazepines, including Ativan (lorazepam), produce increased CNS-depressant effects when administered with other CNS depressants such as alcohol, barbiturates, antipsychotics, sedative/hypnotics, anxiolytics, antidepressants, narcotic analgesics, sedative antihistamines, anticonvulsants, and anesthetics.

Concomitant use of clozapine and lorazepam may produce marked sedation, excessive salivation, hypotension, ataxia, delirium, and respiratory arrest.

Concurrent administration of lorazepam with valproate results in increased plasma concentrations and reduced clearance of lorazepam. Lorazepam dosage should be reduced to approximately 50% when coadministered with valproate.

Concurrent administration of lorazepam with probenecid may result in a more rapid onset or prolonged effect of lorazepam due to increased half-life and decreased total clearance. Lorazepam dosage needs to be reduced by approximately 50% when coadministered with probenecid.

The effects of probenecid and valproate on lorazepam may be due to inhibition of glucuronidation.

Administration of theophylline or aminophylline may reduce the sedative effects of benzodiazepines, including lorazepam.

Carcinogenesis and Mutagenesis

No evidence of carcinogenic potential emerged in rats during an 18-month study with Ativan (lorazepam). No studies regarding mutagenesis have been performed.

Pregnancy

Pregnancy Exposure Registry

There is a pregnancy registry that monitors pregnancy outcomes in women exposed to psychiatric medications, including Ativan, during pregnancy. Healthcare providers are encouraged to register patients by calling the National Pregnancy Registry for Psychiatric Medications at 1-866-961-2388 or visiting online at https://womensmentalhealth.org/pregnancyregistry/.

Risk Summary

Neonates born to mothers using benzodiazepines late in pregnancy have been reported to experience symptoms of sedation and/or neonatal withdrawal (see WARNINGS: Neonatal Sedation and Withdrawal Syndrome and Clinical Considerations). Available data from published observational studies of pregnant women exposed to benzodiazepines do not report a clear association with benzodiazepines and major birth defects (see Data).

The background risk of major birth defects and miscarriage for the indicated population is unknown. All pregnancies have a background risk of birth defect, loss, or other adverse outcomes. In the U.S. general population, the estimated risk of major birth defects and of miscarriage in clinically recognized pregnancies is 2% to 4% and 15% to 20%, respectively.

Clinical Considerations

Fetal/Neonatal Adverse Reactions

Benzodiazepines cross the placenta and may produce respiratory depression, hypotonia and sedation in neonates. Monitor neonates exposed to Ativan during pregnancy or labor for signs of sedation, respiratory depression, hypotonia, and feeding problems. Monitor neonates exposed to Ativan during pregnancy for signs of withdrawal. Manage these neonates accordingly (see WARNINGS: Neonatal Sedation and Withdrawal Syndrome).

Data

Human Data

Published data from observational studies on the use of benzodiazepines during pregnancy do not report a clear association with benzodiazepines and major birth defects. Although early studies reported an increased risk of congenital malformations with diazepam and chlordiazepoxide, there was no consistent pattern noted. In addition, the majority of more recent case-control and cohort studies of benzodiazepine use during pregnancy, which were adjusted for confounding exposures to alcohol, tobacco and other medications, have not confirmed these findings.

Animal Data

Reproductive studies in animals were performed in mice, rats, and two strains of rabbits. Occasional anomalies (reduction of tarsals, tibia, metatarsals, malrotated limbs, gastroschisis, malformed skull, and microphthalmia) were seen in drug-treated rabbits without relationship to dosage. Although all of these anomalies were not present in the concurrent control group, they have been reported to occur randomly in historical controls. At doses of 40 mg/kg and higher, there was evidence of fetal resorption and increased fetal loss in rabbits which was not seen at lower doses.

Nursing Mothers

Risk Summary

Lorazepam is present in breast milk. There are reports of sedation, poor feeding and poor weight gain in infants exposed to benzodiazepines through breast milk. The effects of lorazepam on milk production are unknown. The developmental and health benefits of breastfeeding should be considered along with the mother’s clinical need for Ativan and any potential adverse effects on the breastfed infant from Ativan or from the underlying maternal condition.

Clinical Considerations

Infants exposed to Ativan through breast milk should be monitored for sedation, poor feeding and poor weight gain.

Geriatric Use

Clinical studies of Ativan generally were not adequate to determine whether subjects aged 65 and over respond differently than younger subjects; however, the incidence of sedation and unsteadiness was observed to increase with age (see ADVERSE REACTIONS).

Age does not appear to have a significant effect on lorazepam kinetics (see CLINICAL PHARMACOLOGY).

Clinical circumstances, some of which may be more common in the elderly, such as hepatic or renal impairment, should be considered. Greater sensitivity (e.g., sedation) of some older individuals cannot be ruled out. In general, dose selection for an elderly patient should be cautious, and lower doses may be sufficient in these patients (see DOSAGE AND ADMINISTRATION).

ADVERSE REACTIONS

Most adverse reactions to benzodiazepines, including CNS effects and respiratory depression, are dose dependent, with more severe effects occurring with high doses.

In a sample of about 3500 patients treated for anxiety, the most frequent adverse reaction to Ativan (lorazepam) was sedation (15.9%), followed by dizziness (6.9%), weakness (4.2%), and unsteadiness (3.4%). The incidence of sedation and unsteadiness increased with age.

Other adverse reactions to benzodiazepines, including lorazepam are fatigue, drowsiness, amnesia, memory impairment, confusion, disorientation, depression, unmasking of depression, disinhibition, euphoria, suicidal ideation/attempt, ataxia, asthenia, extrapyramidal symptoms, convulsions/seizures, tremor, vertigo, eye function/visual disturbance (including diplopia and blurred vision), dysarthria/slurred speech, change in libido, impotence, decreased orgasm; headache, coma; respiratory depression, apnea, worsening of sleep apnea, worsening of obstructive pulmonary disease; gastrointestinal symptoms including nausea, change in appetite, constipation, jaundice, increase in bilirubin, increase in liver transaminases, increase in alkaline phosphatase; hypersensitivity reactions, anaphylactoid reactions; dermatological symptoms, allergic skin reactions, alopecia; syndrome of inappropriate antidiuretic hormone (SIADH), hyponatremia; thrombocytopenia, agranulocytosis, pancytopenia; hypothermia; and autonomic manifestations.

Paradoxical reactions, including anxiety, excitation, agitation, hostility, aggression, rage, sleep disturbances/insomnia, sexual arousal, and hallucinations may occur. Small decreases in blood pressure and hypotension may occur but are usually not clinically significant, probably being related to the relief of anxiety produced by Ativan (lorazepam).

To report SUSPECTED ADVERSE REACTIONS, contact Bausch Health US, LLC at 1-800-321-4576 or FDA at 1-800-FDA-1088 or www.fda.gov/medwatch.

DRUG ABUSE AND DEPENDENCE

Controlled Substance

Ativan contains lorazepam, a Schedule IV controlled substance.

Abuse

Ativan is a benzodiazepine and a CNS depressant with a potential for abuse and addiction. Abuse is the intentional, non-therapeutic use of a drug, even once, for its desirable psychological or physiological effects. Misuse is the intentional use, for therapeutic purposes, of a drug by an individual in a way other than prescribed by a healthcare provider or for whom it was not prescribed. Drug addiction is a cluster of behavioral, cognitive, and physiological phenomena that may include a strong desire to take the drug, difficulties in controlling drug use (e.g., continuing drug use despite harmful consequences, giving a higher priority to drug use than other activities and obligations), and possible tolerance or physical dependence. Even taking benzodiazepines as prescribed may put patients at risk for abuse and misuse of their medication. Abuse and misuse of benzodiazepines may lead to addiction.

Abuse and misuse of benzodiazepines often (but not always) involve the use of doses greater than the maximum recommended dosage and commonly involve concomitant use of other medications, alcohol, and/or illicit substances, which is associated with an increased frequency of serious adverse outcomes, including respiratory depression, overdose, or death. Benzodiazepines are often sought by individuals who abuse drugs and other substances, and by individuals with addictive disorders (see WARNINGS: Abuse, Misuse, and Addiction).

The following adverse reactions have occurred with benzodiazepine abuse and/or misuse: abdominal pain, amnesia, anorexia, anxiety, aggression, ataxia, blurred vision, confusion, depression, disinhibition, disorientation, dizziness, euphoria, impaired concentration and memory, indigestion, irritability, muscle pain, slurred speech, tremors, and vertigo.

The following severe adverse reactions have occurred with benzodiazepine abuse and/or misuse: delirium, paranoia, suicidal ideation and behavior, seizures, coma, breathing difficulty, and death. Death is more often associated with polysubstance use (especially benzodiazepines with other CNS depressants such as opioids and alcohol).

Dependence

Physical Dependence

Ativan may produce physical dependence from continued therapy. Physical dependence is a state that develops as a result of physiological adaptation in response to repeated drug use, manifested by withdrawal signs and symptoms after abrupt discontinuation or a significant dose reduction of a drug. Abrupt discontinuation or rapid dosage reduction of benzodiazepines or administration of flumazenil, a benzodiazepine antagonist, may precipitate acute withdrawal reactions, including seizures, which can be life-threatening. Patients at an increased risk of withdrawal adverse reactions after benzodiazepine discontinuation or rapid dosage reduction include those who take higher dosages (i.e., higher and/or more frequent doses) and those who have had longer durations of use (see WARNINGS: Dependence and Withdrawal Reactions).

To reduce the risk of withdrawal reactions, use a gradual taper to discontinue Ativan or reduce the dosage (see DOSAGE AND ADMINISTRATION: Discontinuation or Dosage Reduction of Ativan and WARNINGS).

Acute Withdrawal Signs and Symptoms
Acute withdrawal signs and symptoms associated with benzodiazepines have included abnormal involuntary movements, anxiety, blurred vision, depersonalization, depression, derealization, dizziness, fatigue, gastrointestinal adverse reactions (e.g., nausea, vomiting, diarrhea, weight loss, decreased appetite), headache, hyperacusis, hypertension, irritability, insomnia, memory impairment, muscle pain and stiffness, panic attacks, photophobia, restlessness, tachycardia, and tremor. More severe acute withdrawal signs and symptoms, including life-threatening reactions, have included catatonia, convulsions, delirium tremens, depression, hallucinations, mania, psychosis, seizures and suicidality.
Protracted Withdrawal Syndrome
Protracted withdrawal syndrome associated with benzodiazepines is characterized by anxiety, cognitive impairment, depression, insomnia, formication, motor symptoms (e.g., weakness, tremor, muscle twitches), paresthesia, and tinnitus that persists beyond 4 to 6 weeks after initial benzodiazepine withdrawal. Protracted withdrawal symptoms may last weeks to more than 12 months. As a result, there may be difficulty in differentiating withdrawal symptoms from potential re-emergence or continuation of symptoms for which the benzodiazepine was being used.

Tolerance

Tolerance to Ativan may develop from continued therapy. Tolerance is a physiological state characterized by a reduced response to a drug after repeated administration (i.e., a higher dose of a drug is required to produce the same effect that was once obtained at a lower dose). Tolerance to the therapeutic effect of Ativan may develop; however, little tolerance develops to the amnestic reactions and other cognitive impairments caused by benzodiazepines.

OVERDOSAGE

Overdosage of benzodiazepines is characterized by central nervous system depression ranging from drowsiness to coma. In mild to moderate cases, symptoms can include drowsiness, confusion, dysarthria, lethargy, hypnotic state, diminished reflexes, ataxia, and hypotonia. Rarely, paradoxical or disinhibitory reactions (including agitation, irritability, impulsivity, violent behavior, confusion, restlessness, excitement, and talkativeness) may occur. In severe overdosage cases, patients may develop respiratory depression and coma. Overdosage of benzodiazepines in combination with other CNS depressants (including alcohol and opioids) may be fatal (see WARNINGS: Abuse, Misuse, and Addiction). Markedly abnormal (lowered or elevated) blood pressure, heart rate, or respiratory rate raise the concern that additional drugs and/or alcohol are involved in the overdosage.

In managing benzodiazepine overdosage, employ general supportive measures, including intravenous fluids and airway management. Flumazenil, a specific benzodiazepine receptor antagonist indicated for the complete or partial reversal of the sedative effects of benzodiazepines in the management of benzodiazepine overdosage, can lead to withdrawal and adverse reactions, including seizures, particularly in the context of mixed overdosage with drugs that increase seizure risk (e.g., tricyclic and tetracyclic antidepressants) and in patients with long-term benzodiazepine use and physical dependency. The risk of withdrawal seizures with flumazenil use may be increased in patients with epilepsy. Flumazenil is contraindicated in patients who have received a benzodiazepine for control of a potentially life-threatening condition (e.g., status epilepticus). If the decision is made to use flumazenil, it should be used as an adjunct to, not as a substitute for, supportive management of benzodiazepine overdosage. See the flumazenil injection Prescribing Information.

Consider contacting the Poison Help line (1-800-222-1222) or a medical toxicologist for additional overdosage management recommendations.

DOSAGE AND ADMINISTRATION

Ativan (lorazepam) is administered orally. For optimal results, dose, frequency of administration, and duration of therapy should be individualized according to patient response. To facilitate this, 0.5 mg, 1 mg, and 2 mg tablets are available.

The usual range is 2 to 6 mg/day given in divided doses, the largest dose being taken before bedtime, but the daily dosage may vary from 1 to 10 mg/day.

For anxiety, most patients require an initial dose of 2 to 3 mg/day given two times a day or three times a day.

For insomnia due to anxiety or transient situational stress, a single daily dose of 2 to 4 mg may be given, usually at bedtime.

For elderly or debilitated patients, an initial dosage of 1 to 2 mg/day in divided doses is recommended, to be adjusted as needed and tolerated.

The dosage of Ativan (lorazepam) should be increased gradually when needed to help avoid adverse effects. When higher dosage is indicated, the evening dose should be increased before the daytime doses.

Discontinuation or Dosage Reduction of Ativan

To reduce the risk of withdrawal reactions, use a gradual taper to discontinue Ativan or reduce the dosage. If a patient develops withdrawal reactions, consider pausing the taper or increasing the dosage to the previous tapered dosage level. Subsequently decrease the dosage more slowly (see WARNINGS: Dependence and Withdrawal Reactions and DRUG ABUSE AND DEPENDENCE: Dependence).

HOW SUPPLIED

Ativan® (lorazepam) Tablets are available in the following dosage strengths:

0.5 mg, white, five-sided (shield shape) tablet with a raised “A” on one side and “BPI” and “63” impressed on reverse side.

NDC 0187-0063-01 - Bottles of 100 tablets.

1 mg, white, five-sided (shield shape) tablet with a raised “A” on one side and “BPI” and “64” impressed on scored reverse side.

NDC 0187-0064-01 - Bottles of 100 tablets.

2 mg, white, five-sided (regular pentagon) tablet with a raised “A” and impressed “2” on one side and “BPI” and “65” impressed on scored reverse side.

NDC 0187-0065-01 - Bottles of 100 tablets.

Keep bottles tightly closed.
Keep out of reach of children.

Store at 25°C (77°F); excursions permitted to 15° to 30°C (59° to 86°F) [see USP Controlled Room Temperature].

Dispense in a tight container.

Distributed by:
Bausch Health US, LLC
Bridgewater, NJ 08807 USA
Manufactured by:
Bausch Health Companies Inc.
Steinbach, MB R5G 1Z7, Canada
Ativan is a registered trademark of Bausch Health Companies Inc. or its affiliates.

© 2025 Bausch Health Companies Inc. or its affiliates

Rev. 07/2025 9644304 20005922

Medication Guide

ATIVAN (AT-ivan)

(lorazepam) Tablets

What is the most important information I should know about ATIVAN?

- ATIVAN is a benzodiazepine medicine. Taking benzodiazepines with opioid medicines, alcohol, or other central nervous system depressants (including street drugs) can cause severe drowsiness, breathing problems (respiratory depression), coma and death. Get emergency help right away if any of the following happens:
  - shallow or slowed breathing
  - breathing stops (which may lead to the heart stopping)
  - excessive sleepiness (sedation)

Do not drive or operate heavy machinery until you know how taking ATIVAN with opioids

affects you.

- Risk of abuse, misuse, and addiction. There is a risk of abuse, misuse, and addiction with benzodiazepines including ATIVAN which can lead to overdose and serious side effects including coma and death.
  - Serious side effects including coma and death have happened in people who have abused or misused benzodiazepines, including ATIVAN. These serious side effects may also include delirium, paranoia, suicidal thoughts or actions, seizures, and difficulty breathing. Call your healthcare provider or go to the nearest hospital emergency room right away if you get any of these serious side effects.
  - You can develop an addiction even if you take ATIVAN exactly as prescribed by your healthcare provider.
  - Take ATIVAN exactly as your healthcare provider prescribed.
  - Do not share your ATIVAN with other people.
  - Keep ATIVAN in a safe place and away from children.
- Physical dependence and withdrawal reactions. ATIVAN can cause physical dependence and withdrawal reactions.
  - Do not suddenly stop taking ATIVAN. Stopping ATIVAN suddenly can cause serious and life-threatening side effects, including, unusual movements, responses or expressions, seizures, sudden and severe mental or nervous system changes, depression, seeing or hearing things that others do not see or hear, an extreme increase in activity or talking, losing touch with reality, and suicidal thoughts or actions. Call your healthcare provider or go to the nearest hospital emergency room right away if you get any of these symptoms.
  - Some people who suddenly stop benzodiazepines have symptoms that can last for several weeks to more than 12 months, including anxiety, trouble remembering, learning, or concentrating, depression, problems sleeping, feeling like insects are crawling under your skin, weakness, shaking, muscle twitching, burning or prickling feeling in your hands, arms, legs or feet, and ringing in your ears.
  - Physical dependence is not the same as drug addiction. Your healthcare provider can tell you more about the differences between physical dependence and drug addiction.
- Do not take more ATIVAN than prescribed or take ATIVAN for longer than prescribed.

What is ATIVAN?

- ATIVAN is a prescription medicine used:
  - to treat anxiety disorders
  - for the short-term relief of the symptoms of anxiety or anxiety that can happen with symptoms of depression
- ATIVAN is a federal controlled substance (CIV) because it contains lorazepam that can be abused or lead to dependence. Keep ATIVAN in a safe place to prevent misuse and abuse. Selling or giving away ATIVAN may harm others, and is against the law. Tell your healthcare provider if you have abused or been dependent on alcohol, prescription medicines or street drugs.
- It is not known if ATIVAN is safe and effective for use in children less than 12 years of age.
- It is not known if ATIVAN is safe and effective for use for longer than 4 months.

Do not take ATIVAN if you:

- are allergic to lorazepam, other benzodiazepines, or any of the ingredients in ATIVAN. See the end of this Medication Guide for a complete list of ingredients in ATIVAN.

Before you take ATIVAN, tell your healthcare provider about all of your medical conditions, including if you:

- have or have had depression, mood problems, or suicidal thoughts or behavior
- have a history of drug or alcohol abuse or addiction
- have lung disease or breathing problems (such as COPD, sleep apnea syndrome)
- have liver or kidney problems
- have or have had seizures
- are pregnant or plan to become pregnant
- Taking ATIVAN late in pregnancy may cause your baby to have symptoms of sedation (breathing problems, sluggishness, low muscle tone), and/or withdrawal symptoms (jitteriness, irritability, restlessness, shaking, excessive crying, feeding problems).
- Tell your healthcare provider right away if you become pregnant or think you are pregnant during treatment with ATIVAN.
- There is a pregnancy registry for women who take ATIVAN during pregnancy. The purpose of the registry is to collect information about the health of you and your baby. If you become pregnant during treatment with ATIVAN, talk to your healthcare provider about registering with the National Pregnancy Registry for Psychiatric Medications. You can register by calling 1-866-961-2388 or visiting https://womensmentalhealth.org/pregnancyregistry/.
- are breastfeeding or plan to breastfeed. ATIVAN passes into your breast milk
- Breastfeeding during treatment with ATIVAN may cause your baby to have sleepiness, feeding problems, and decreased weight gain.
- Talk to your healthcare provider about the best way to feed your baby if you take ATIVAN.

Tell your healthcare provider about all the medicines you take, including prescription and over-the-counter medicines, vitamins, and herbal supplements.

Taking ATIVAN with certain other medicines can cause side effects or affect how well ATIVAN or the other medicines work. Do not start or stop other medicines without talking to your healthcare provider.

How should I take ATIVAN?

- Take ATIVAN exactly as your healthcare provider tells you to take it. Your healthcare provider will tell you how much ATIVAN to take and when to take it.
- If you take too much ATIVAN, call your healthcare provider or go to the nearest hospital emergency room right away.

What are the possible side effects of ATIVAN?

ATIVAN may cause serious side effects, including:

- See “What is the most important information I should know about ATIVAN?”
- ATIVAN can make you sleepy or dizzy and can slow your thinking and motor skills.
  - Do not drive, operate heavy machinery, or do other dangerous activities until you know how ATIVAN affects you.
  - Do not drink alcohol or take other drugs that may make you sleepy or dizzy while taking ATIVAN without first talking to your healthcare provider. When taken with alcohol or drugs that cause sleepiness or dizziness, ATIVAN may make your sleepiness or dizziness much worse.
- Depression. Pre-existing depression may emerge or worsen during use of benzodiazepines including ATIVAN.

The most common side effects of ATIVAN include:

• sedation • dizziness

• weakness • unsteadiness

These are not all the possible side effects of ATIVAN. Call your doctor for medical advice about side effects. You may report side effects to FDA at 1-800-FDA-1088.

How should I store ATIVAN?

- Store ATIVAN in a tightly closed container at room temperature between 68°F to 77°F (20°C to 25°C).
- Keep ATIVAN and all medicines out of the reach of children.

General information about the safe and effective use of ATIVAN

Medicines are sometimes prescribed for purposes other than those listed in a Medication Guide. Do not use ATIVAN for a condition for which it was not prescribed. Do not give ATIVAN to other people, even if they have the same symptoms that you have. It may harm them. You can ask your pharmacist or healthcare provider for information about ATIVAN that is written for health professionals.

What are the ingredients in ATIVAN?

Active ingredient: lorazepam

Inactive ingredients: lactose monohydrate, magnesium stearate, microcrystalline cellulose, and polacrilin potassium.

Distributed by: Bausch Health US, LLC
Bridgewater, NJ 08807 USA
Manufactured by: Bausch Health Companies Inc.
Steinbach, MB R5G 1Z7, Canada

ATIVAN is a registered trademark of Bausch Health Companies Inc. or its affiliates. For more information, call 1-800-321-4576.

© 2025 Bausch Health Companies Inc. or its affiliates

This Medication Guide has been approved by the U.S. Food and Drug Administration.

Revised: 07/2025

9644304 20005922

PRINCIPAL DISPLAY PANEL - 2.0 mg Bottle Label

NDC 0187-0065-01

Rx only

Ativan®
(lorazepam) Tablets

CIV
SEALED
FOR YOUR
PROTECTION

2 mg

PHARMACIST: Dispense the accompanying Medication Guide to each patient.

100 Tablets

BAUSCH Health

Package/Label Display Panel

NDC 0187-0064-01

Rx only

Ativan®
(lorazepam) Tablets

CIV
SEALED
FOR YOUR
PROTECTION

1 mg

PHARMACIST: Dispense the accompanying Medication Guide to each patient.

100 Tablets

BAUSCH Health

Package/Label Display Panel 0.5 mg Bottle Label

NDC0187-0063-01

Rx only

Ativan®
(lorazepam) Tablets

CIV
SEALED
FOR YOUR
PROTECTION

0.5 mg

PHARMACIST: Dispense the accompanying Medication Guide to each patient.

100 Tablets

BAUSCH Health